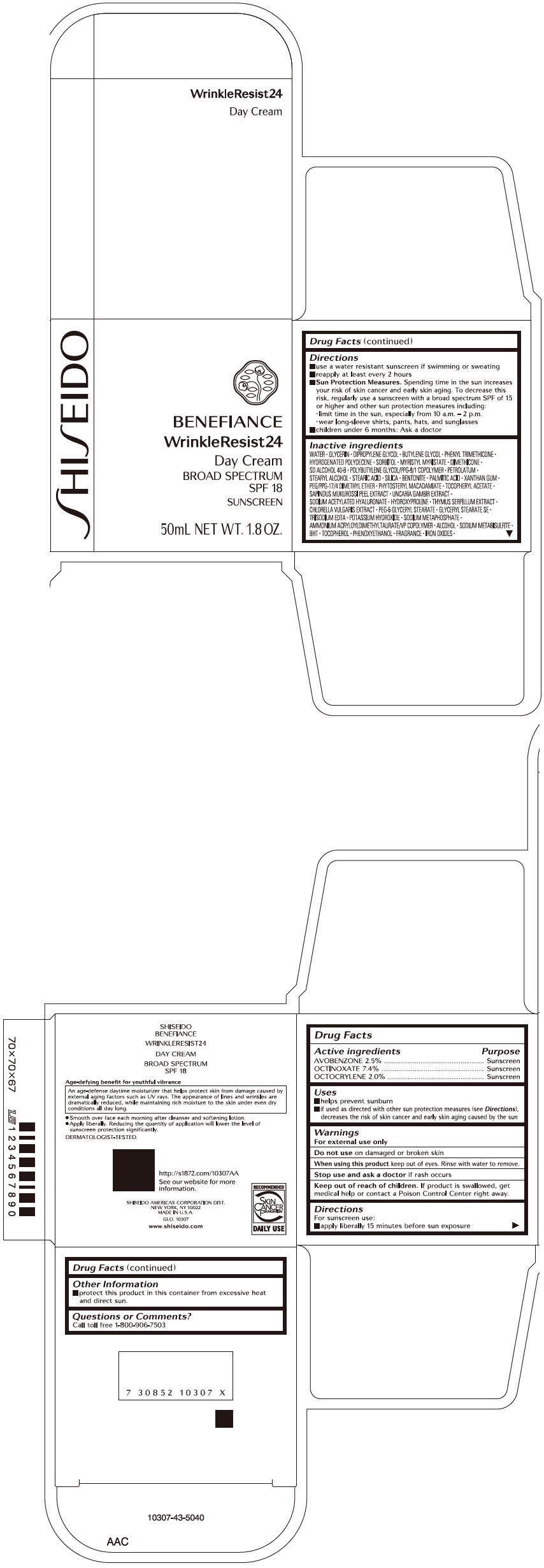 DRUG LABEL: SHISEIDO BENEFIANCE WRINKLERESIST24 DAY
NDC: 58411-629 | Form: CREAM
Manufacturer: SHISEIDO AMERICAS CORPORATION
Category: otc | Type: HUMAN OTC DRUG LABEL
Date: 20260106

ACTIVE INGREDIENTS: AVOBENZONE 1.28 g/50 mL; OCTINOXATE 3.85 g/50 mL; OCTOCRYLENE 1.02 g/50 mL
INACTIVE INGREDIENTS: WATER; GLYCERIN; DIPROPYLENE GLYCOL; BUTYLENE GLYCOL; PHENYL TRIMETHICONE; HYDROGENATED POLYDECENE TYPE I; SORBITOL; MYRISTYL MYRISTATE; DIMETHICONE; PETROLATUM; STEARYL ALCOHOL; STEARIC ACID; SILICON DIOXIDE; BENTONITE; PALMITIC ACID; XANTHAN GUM; PEG/PPG-17/4 DIMETHYL ETHER; PHYTOSTERYL MACADAMIATE; .ALPHA.-TOCOPHEROL ACETATE, DL-; SAPINDUS MUKOROSSI FRUIT RIND; SODIUM ACETYLATED HYALURONATE; HYDROXYPROLINE; CHLORELLA VULGARIS; PEG-5 GLYCERYL STEARATE; GLYCERYL MONOSTEARATE; EDETATE TRISODIUM; POTASSIUM HYDROXIDE; SODIUM POLYMETAPHOSPHATE; AMMONIUM ACRYLOYLDIMETHYLTAURATE/VP COPOLYMER; ALCOHOL; SODIUM METABISULFITE; BUTYLATED HYDROXYTOLUENE; .ALPHA.-TOCOPHEROL; PHENOXYETHANOL; FERRIC OXIDE RED; FERRIC OXIDE YELLOW; FERROSOFERRIC OXIDE

SHISEIDO BENEFIANCE WRINKLERESIST24 DAY CREAM

Drug Facts

ACTIVE INGREDIENT

Active ingredients | Purpose
AVOBENZON 2.5 % | Sunscreen
OCTINOXATE 7.4 % | Sunscreen
OCTOCRYLENE 2.0 % | Sunscreen

Uses

- helps prevent sunburn
- if used as directed with other sun protection measures (see Directions), decreases the risk of skin cancer and early skin aging caused by the sun

Warnings

For external use only

Do not use on damaged or broken skin

WHEN USING

When using this productkeep out of eyes. Rinse with water to remove.

Stop use and ask a doctorif rash occurs.

Keep out of reach of children.If product is swallowed, get medical help or contact a Poison Control Center right away.

Directions

For sunscreen use:

- apply liberally 15 minutes before sun exposure
- use a water resistant sunscreen if swimming or sweating
- reapply at least every two hours
- Sun Protection Measures.
  Spending time in the sun increases your risk of skin cancer and early skin aging. To decrease this risk, regularly use a sunscreen with a broad spectrum SPF of 15 or higher and other sun protection measures including:
  - limit time in the sun, especially from 10 a.m. – 2 p.m.
  - wear long-sleeve shirts, pants, hats, and sunglasses
- children under 6 months: Ask a doctor

Inactive Ingredients

WATER∙GLYCERIN∙DIPROPYLENE GLYCOL∙BUTYLENE GLYCOL∙PHENYL TRIMETHICONE∙HYDROGENATED POLYDECENE∙SORBITOL∙MYRISTYL MYRISTATE∙DIMETHICONE∙SD ALCOHOL 40-B∙POLYBUTYLENE GLYCOL/PPG-9/1 COPOLYMER∙PETROLATUM∙STEARYL ALCOHOL∙STEARIC ACID∙SILICA∙BENTONITE∙PALMITIC ACID∙XANTHAN GUM∙PEG/PPG-17/4 DIMETHYL ETHER∙PHYTOSTERYL MACADAMIATE∙TOCOPHERYL ACETATE∙SAPINDUS MUKUROSSI PEEL EXTRACT∙UNCARIA GAMBIR EXTRACT∙SODIUM ACETYLATED HYALURONATE∙HYDROXYPROLINE∙THYMUS SERPILLUM EXTRACT∙CHLORELLA VULGARIS EXTRACT∙PEG-5 GLYCERYL STEARATE∙GLYCERYL STEARATE SE∙TRISODIUM EDTA∙POTASSIUM HYDROXIDE∙SODIUM METAPHOSPHATE∙AMMONIUM ACRYLOYLDIMETHYLTAURATE/VP COPOLYMER∙ALCOHOL∙SODIUM METABISULFITE∙BHT∙TOCOPHEROL∙PHENOXYETHANOL∙FRAGRANCE∙IRON OXIDES∙

Other information

Protect this product in this container from excessive heat and direct sun.

Questions or comments?

Call toll free 1-800-906-7503

PRINCIPAL DISPLAY PANEL - 50 mL Bottle Carton

SHISEIDO

BENEFIANCE
WrinkleResist24
Day Cream
BROAD SPECTRUM
SPF 18
SUNSCREEN

50mL NET WT. 1.8 OZ.